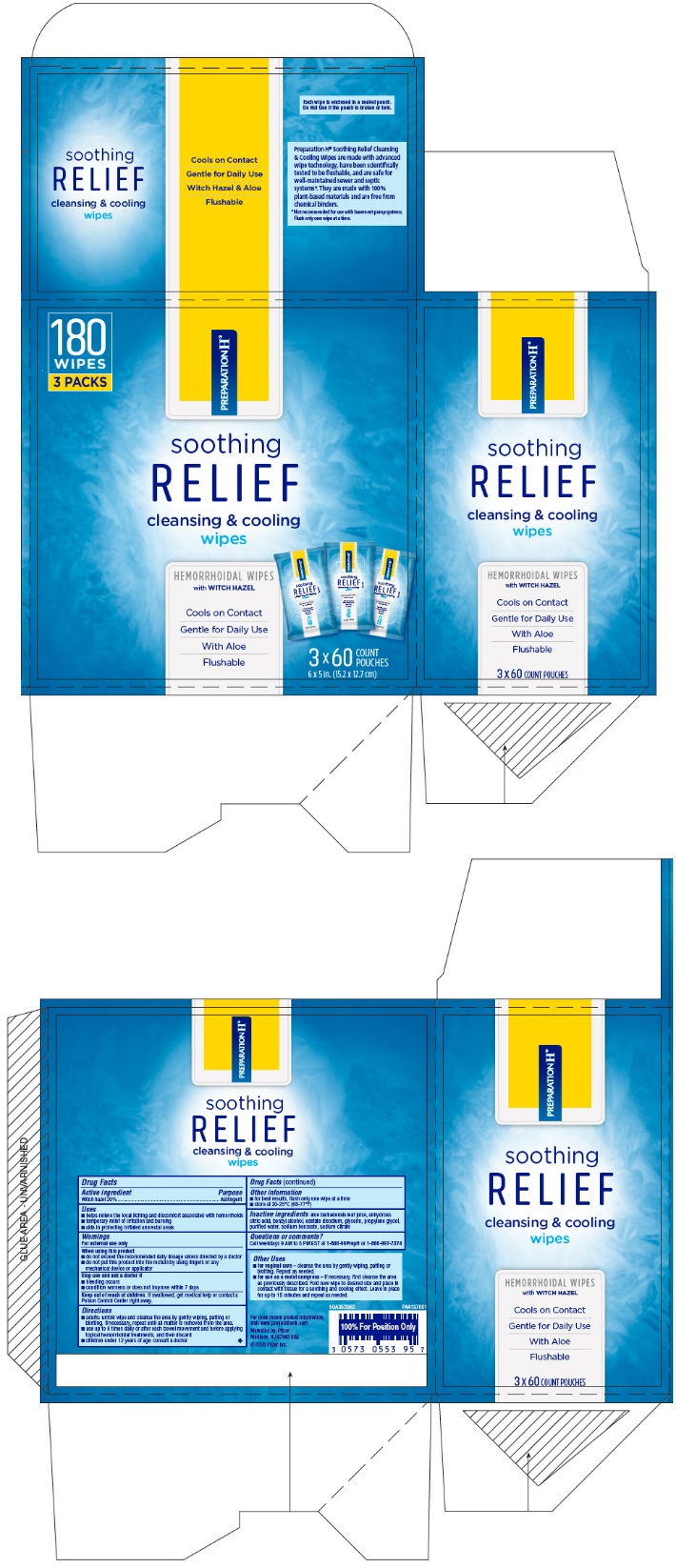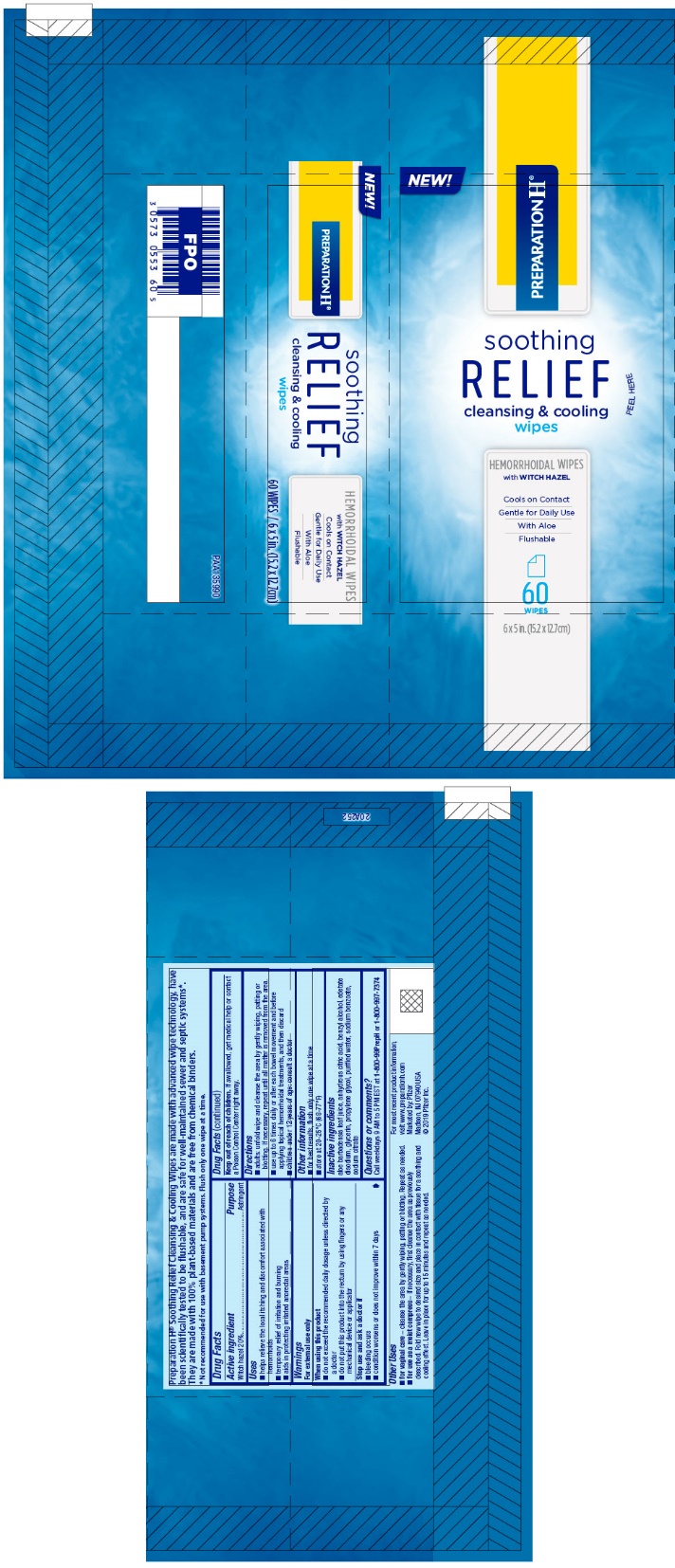 DRUG LABEL: PREPARATION H SOOTHING RELIEF CLEANSING AND COOLING WIPES
NDC: 0573-0553 | Form: CLOTH
Manufacturer: Haleon US Holdings LLC
Category: otc | Type: HUMAN OTC DRUG LABEL
Date: 20250707

ACTIVE INGREDIENTS: WITCH HAZEL 200 mg/1 1
INACTIVE INGREDIENTS: ALOE VERA LEAF; ANHYDROUS CITRIC ACID; GLYCERIN; PROPYLENE GLYCOL; SODIUM CITRATE, UNSPECIFIED FORM; WATER; BENZYL ALCOHOL; EDETATE DISODIUM; SODIUM BENZOATE

Drug Facts

Drug Facts

Active ingredient

Witch hazel 20%

Purpose

Astringent

Uses

- helps relieve the local itching and discomfort associated with hemorrhoids
- temporary relief of irritation and burning
- aids in protecting irritated anorectal areas

Warnings

For external use only

When using this product

- do not exceed the recommended daily dosage unless directed by a doctor
- do not put this product into the rectum by using fingers or any mechanical device or applicator

Stop use and ask a doctor if

- bleeding occurs
- condition worsens or does not improve within 7 days

Keep out of reach of children.If swallowed, get medical help or contact a Poison Control Center right away.

Directions

- adults: unfold wipe and cleanse the area by gently wiping, patting or blotting. If necessary, repeat until all matter is removed from the area.
- use up to 6 times daily or after each bowel movement and before applying topical hemorrhoidal treatments, and then discard
- children under 12 years of age: consult a doctor

Other information

- for best results, flush only one wipe at a time
- store at 20-25°C (68-77°F)

Inactive ingredients

aloe barbadensis leaf juice, anhydrous citric acid, benzyl alcohol, edetate disodium, glycerin, propylene glycol, purified water, sodium benzoate, sodium citrate

Questions or comments?

Call weekdays 9 AM to 5 PM EST at 1-800-99PrepHor 1-800-997-7374

PRINCIPAL DISPLAY PANEL - 60 Wipe Pouch Carton

180
WIPES
3 PACKS

PREPARATION H®

soothing
RELIEF
cleansing & cooling
wipes

HEMORRHOIDAL WIPES
with WITCH HAZEL

Cools on Contact
Gentle for Daily Use
With Aloe
Flushable

3 x 60
COUNT
POUCHES
6 x 5 in. (15.2 x 12.7 cm)

PRINCIPAL DISPLAY PANEL - 60 Wipe Pouch

NEW!

PREPARATION H®

soothing
RELIEF
cleansing & cooling
wipes
PEEL HERE

HEMORRHOIDAL WIPES
with WITCH HAZEL

Cools on Contact
Gentle for Daily Use
With Aloe
Flushable

60
WIPES

6 x 5 in. (15.2 x 12.7cm)